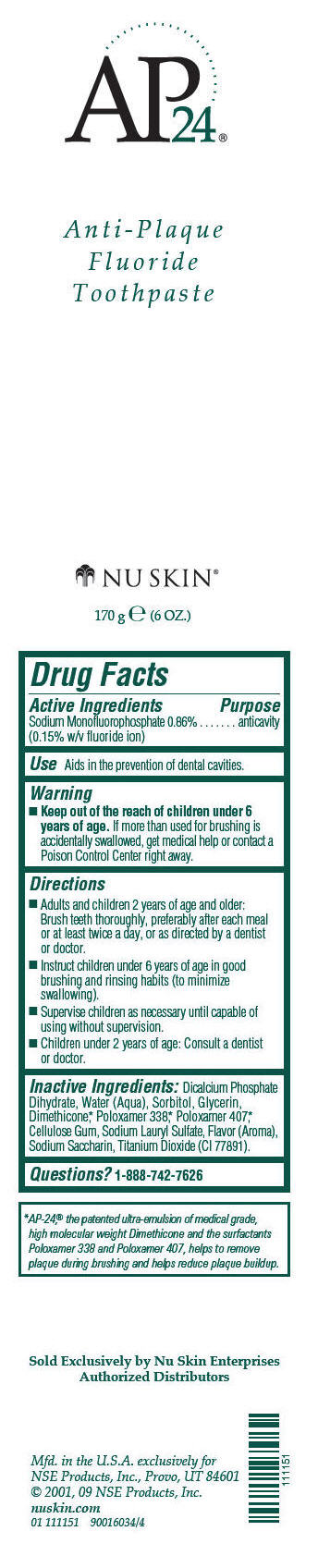 DRUG LABEL: AP-24 Fluoride
NDC: 62839-1151 | Form: PASTE
Manufacturer: NSE Products, Inc
Category: otc | Type: HUMAN OTC DRUG LABEL
Date: 20241227

ACTIVE INGREDIENTS: SODIUM MONOFLUOROPHOSPHATE 8.6 mg/1 g
INACTIVE INGREDIENTS: DIBASIC CALCIUM PHOSPHATE DIHYDRATE; Water; Sorbitol; Dimethicone; Poloxamer 338; Poloxamer 407; Glycerin; CARBOXYMETHYLCELLULOSE SODIUM, UNSPECIFIED; Sodium Lauryl Sulfate; SACCHARIN SODIUM; Titanium Dioxide

AP-24® Fluoride Toothpaste

Drug Facts

Active Ingredients

Sodium Monofluorophosphate 0.86% (0.15% w/v fluoride ion)

Purpose

anticavity

Use

Aids in the prevention of dental cavities.

Warning

KEEP OUT OF REACH OF CHILDREN

- Keep out of the reach of children under 6 years of age. If more than used for brushing is accidentally swallowed, get medical help or contact a Poison Control Center right away.

Directions

- Adults and children 2 years of age and older: Brush teeth thoroughly, preferably after each meal or at least twice a day, or as directed by a dentist or doctor.
- Instruct children under 6 years of age in good brushing and rinsing habits (to minimize swallowing).
- Supervise children as necessary until capable of using without supervision.
- Children under 2 years of age: Consult a dentist or doctor.

Inactive Ingredients

Dicalcium Phosphate Dihydrate, Water (Aqua), Sorbitol, Glycerin, Dimethicone, [AP-24,® the patented ultra-emulsion of medical grade, high molecular weight Dimethicone and the surfactants Poloxamer 338 and Poloxamer 407, helps to remove plaque during brushing and helps reduce plaque buildup.] Poloxamer 338, Poloxamer 407, Cellulose Gum, Sodium Lauryl Sulfate, Flavor (Aroma), Sodium Saccharin, Titanium Dioxide (CI 77891).

Questions?

1-888-742-7626

PRINCIPAL DISPLAY PANEL - 170 g Tube Label

AP24®

Anti-Plaque
Fluoride
Toothpaste

NU SKIN®

170 g e (6 OZ.)